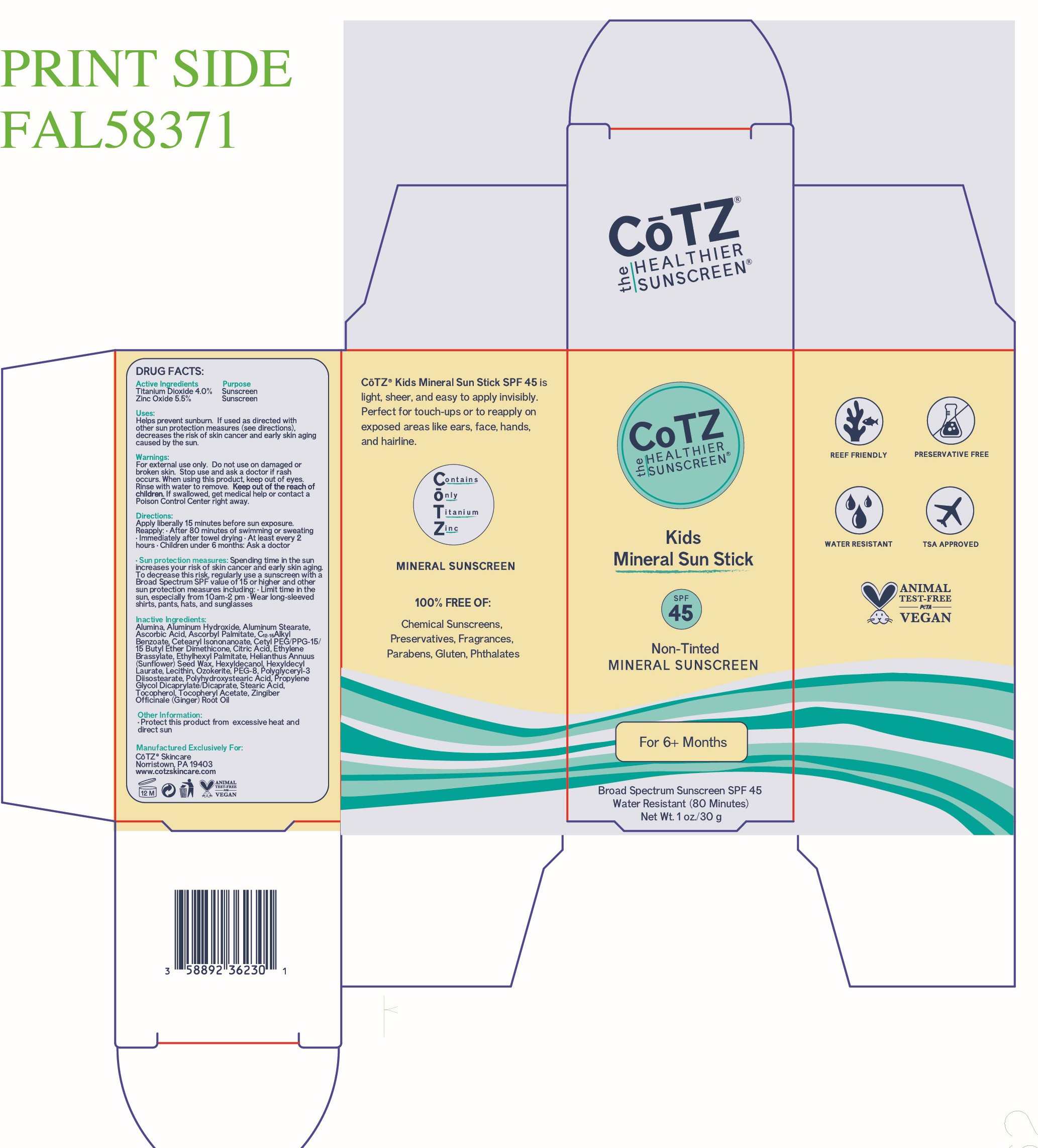 DRUG LABEL: CoTZ Kids Mineral Sun Stick
NDC: 58892-362 | Form: STICK
Manufacturer: Fallien Cosmeceuticals, LTD
Category: otc | Type: HUMAN OTC DRUG LABEL
Date: 20250303

ACTIVE INGREDIENTS: ZINC OXIDE 55 mg/1 g; TITANIUM DIOXIDE 40 mg/1 g
INACTIVE INGREDIENTS: ALUMINUM HYDROXIDE; HEXYLDECANOL; PEG-8; POLYHYDROXYSTEARIC ACID (2300 MW); STEARIC ACID; TOCOPHEROL; HEXYLDECYL LAURATE; PROPYLENE GLYCOL DICAPRYLATE/DICAPRATE; PEG/PPG-15/15 DIMETHICONE; ETHYLHEXYL PALMITATE; POLYGLYCERYL-3 DIISOSTEARATE; CERESIN; ASCORBIC ACID; HELIANTHUS ANNUUS (SUNFLOWER) SEED WAX; LECITHIN, SOYBEAN; CETEARYL ISONONANOATE; ALUMINUM STEARATE; ETHYLENE BRASSYLATE; CETYL DIMETHYLBUTYL ETHER; ALUMINA; C12-15 ALKYL BENZOATE; CITRIC ACID; ZINGIBER OFFICINALE (GINGER) ROOT OIL; ALPHA-TOCOPHEROL ACETATE; ASCORBYL PALMITATE

Active Ingredients:

Titanium Dioxide 4% Zinc Oxide 5.5%

Purpose

Sunscreen

Uses:

Helps prevent sunburn. If used as directed with other sun protection measures (see directions), decreases the risk of skin cancer and early skin aging caused by the sun.

Warnings:

For external use only. Do not use on damaged or broken skin. Stop use and ask a doctor if rash occurs. When using this product, keep out of eyes. Rinse with water to remove. Keep out of the reach of children. If swallowed, get medical help or contact a poison control center right away.

Directions:

Apply liberally 15 minutes before sun exposure. Reapply: After 80 minutes of swimming or sweating - immediately after towel drying - At least every 2 hours - Children under 6 months: Ask a doctor.

Inactive Ingredients:

Alumina, Aluminum Hydroxide, Aluminum Stearate, Ascorbic Acid, Ascorbyl Palmitate, C12-15 Alkyl Benzoate, Cetearyl Isononanoate, Cetyl PEG/PPG-15/15 Butyl Ether Dimethicone, Citric Acid, Ethylene Brassylate, Ethylhexyl Palmitate, Helianthus Annuus (Sunflower) Wax, Hexyldecanol, Hexyldecyl Laurate, Lecithin, Ozokerite, PEG-8, Polyglyceryl-3 Diisostearate, Polyhydroxystearic Acid, Propylene Glycol Dicaprylate/Dicaprate, Stearic Acid, Tocopherol, Tocopheryl Acetate, Zingiber Officinale (Ginger) Root Oil

Other Information:

Protect this product from excessive heat and direct sun.

Warning:

Keep out of the reach of children.